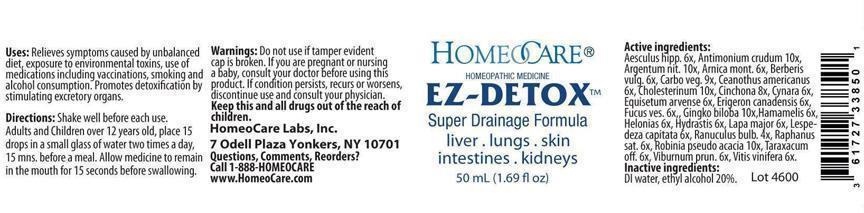 DRUG LABEL: EZ-Detox Super Drainage Formula
NDC: 61727-338 | Form: LIQUID
Manufacturer: Homeocare Laboratories
Category: homeopathic | Type: HUMAN OTC DRUG LABEL
Date: 20181231

ACTIVE INGREDIENTS: AESCULUS HIPPOCASTANUM BARK 6 [hp_X]/50 mL; ANTIMONY TRISULFIDE 10 [hp_X]/50 mL; SILVER NITRATE 10 [hp_X]/50 mL; ARNICA MONTANA 6 [hp_X]/50 mL; BERBERIS VULGARIS WHOLE 6 [hp_X]/50 mL; ACTIVATED CHARCOAL 9 [hp_X]/50 mL; CEANOTHUS AMERICANUS WHOLE 6 [hp_X]/50 mL; CHOLESTEROL 10 [hp_X]/50 mL; CINCHONA BARK 8 [hp_X]/50 mL; CYNARA SCOLYMUS LEAF 6 [hp_X]/50 mL; EQUISETUM ARVENSE TOP 6 [hp_X]/50 mL; CONYZA CANADENSIS 6 [hp_X]/50 mL; FUCUS VESICULOSUS 6 [hp_X]/50 mL; GINKGO 10 [hp_X]/50 mL; HAMAMELIS VIRGINIANA LEAF 6 [hp_X]/50 mL; CHAMAELIRIUM LUTEUM ROOT 6 [hp_X]/50 mL; GOLDENSEAL 6 [hp_X]/50 mL; ARCTIUM LAPPA ROOT 6 [hp_X]/50 mL; LESPEDEZA CAPITATA FLOWERING TOP 6 [hp_X]/50 mL; RANUNCULUS BULBOSUS 4 [hp_X]/50 mL; DAIKON 6 [hp_X]/50 mL; ROBINIA PSEUDOACACIA BARK 10 [hp_X]/50 mL; TARAXACUM PALUSTRE ROOT 6 [hp_X]/50 mL; VIBURNUM PRUNIFOLIUM BARK 6 [hp_X]/50 mL; VITIS VINIFERA WHOLE 6 [hp_X]/50 mL
INACTIVE INGREDIENTS: WATER; ALCOHOL

EZ-Detox-Super Drainage Formula

Active Ingredients:

Aesculus hipp. 6x, Antimonium crudum 10x, Argentum nit. 10x, Arnica mont. 6x, Berberis vulg. 6x, Carbo veg. 9x, Ceonothus americanus 6x, Cholesterinum 10x, Cinchona 8x, Cynara 6x, Equisetum arvense 6x, Erigeron canadensis 6x, Fucus ves. 6x, Gingko biloba 10x, Hamamelis 6x, Helonias 6x, Hydrastis 6x, Lapa major 6x, Lespedeza capitata 6x, Ranuculus bulb.4x, Raphanus sat. 6x, Robinia pseudo acacia 10x, Taraxacum off. 6x, Viburnum prun. 6x, Vitis vinifera 6x.

Inactive Ingredients:

DI water, ethyl alcohol 20%.

Purpose:

Relieves symptoms caused by unbalanced diet, exposure to environmental toxins, use of medications including vaccinations, smoking and alcohol consumption. Promotes detoxification by stimulating excretory organs.

Warnings:

Do not use if tamper evident cap is broken. If you are pregnant or nursing a baby, consult your doctor before using this product. If condition persists, recurs or worsens, discontinue use and consult your physician.

Indications & Usage:

Shake well before each use. Adults and Children over 12 years, place 15 drops in a small glass of water two times a day, 15 mns. before a meal. Allow medicine to remain in the mouth for 15 seconds before swallowing.

Dosage & Administration:

Shake well before each use. Adults and Children over 12 years, place 15 drops in a small glass of water two times a day, 15 mns. before a meal. Allow medicine to remain in the mouth for 15 seconds before swallowing.

Keep out of reach of children.

EZ-Detox Super Drainage Formula

Homeopathic Medicine

EZ-Detox Super Drainage Formula

liver.lungs.skin

intestines.kidneys

50 ml (1.69 fl oz)

EZ-Detox-Super-Drainage-Formula-2.jpg